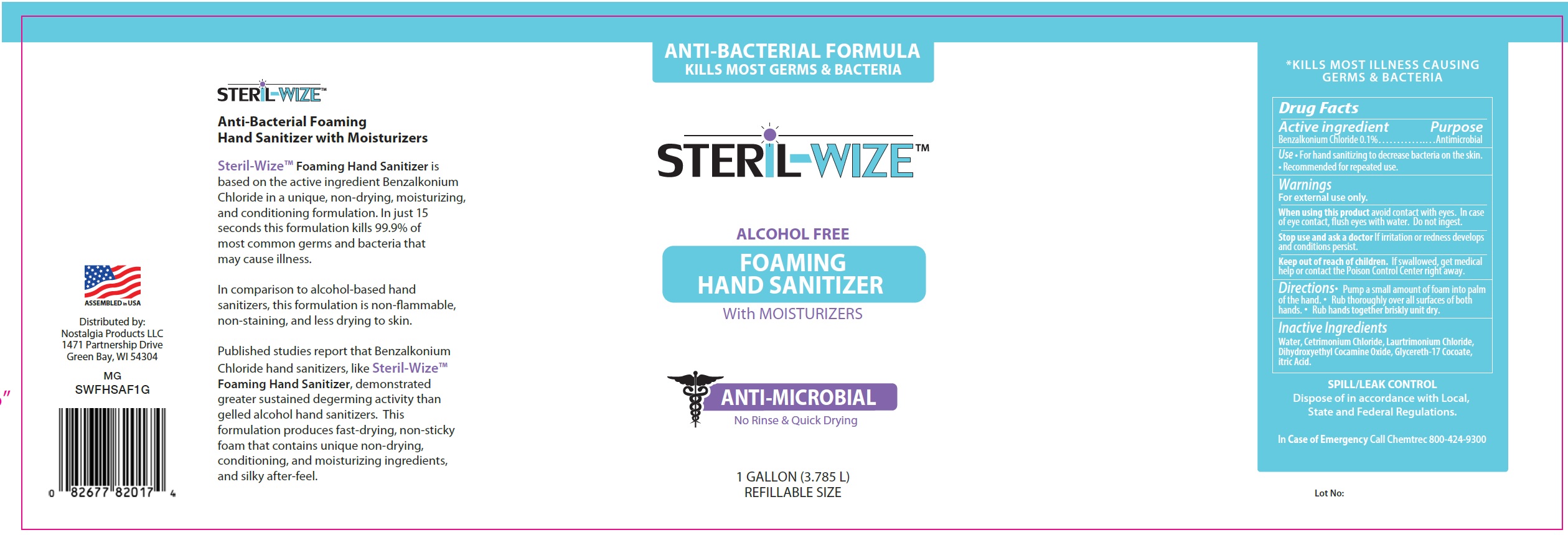 DRUG LABEL: Steril Wize Antibacterial Foaming Hand Sanitizer
NDC: 77051-004 | Form: SOLUTION
Manufacturer: Nostalgia Products LLC
Category: otc | Type: HUMAN OTC DRUG LABEL
Date: 20200707

ACTIVE INGREDIENTS: BENZALKONIUM CHLORIDE 1 mg/1 mL
INACTIVE INGREDIENTS: WATER; CETRIMONIUM CHLORIDE; LAURTRIMONIUM CHLORIDE; DIHYDROXYETHYL COCAMINE OXIDE; GLYCERETH-17 COCOATE; CITRIC ACID MONOHYDRATE

Steril-Wize Anti-Bacterial Foaming Hand Sanitizer

Active ingredient

Benzalkonium Chloride 0.1%

Purpose

Antimicrobial

Use

- For hand sanitizing to decrease bacteria on the skin.
- Recommended for repeated use.

Warnings

For external use only.

When using this product

If irritation or redness develops and conditions persist.

Stop use and ask a doctor

If irritation or redness develops and conditions persist.

Keep out of reach of children.

If swallowed, get medical help or contact a Poison Control Center right away.

Directions

- Pump a small amount of foam into palm of the hand.
- Rub thoroughly over all surfaces of both hands.
- Rub hands together briskly unit dry.

Inactive Ingredients

Water, Cetrimonium Chloride, Laurtrimonium Chloride, Dihydroxyethyl Cocamine Oxide, Glycereth-17 Cocoate, itric Acid.

QUESTIONS

In Case of Emergency Call Chemtrec 800-424-9300